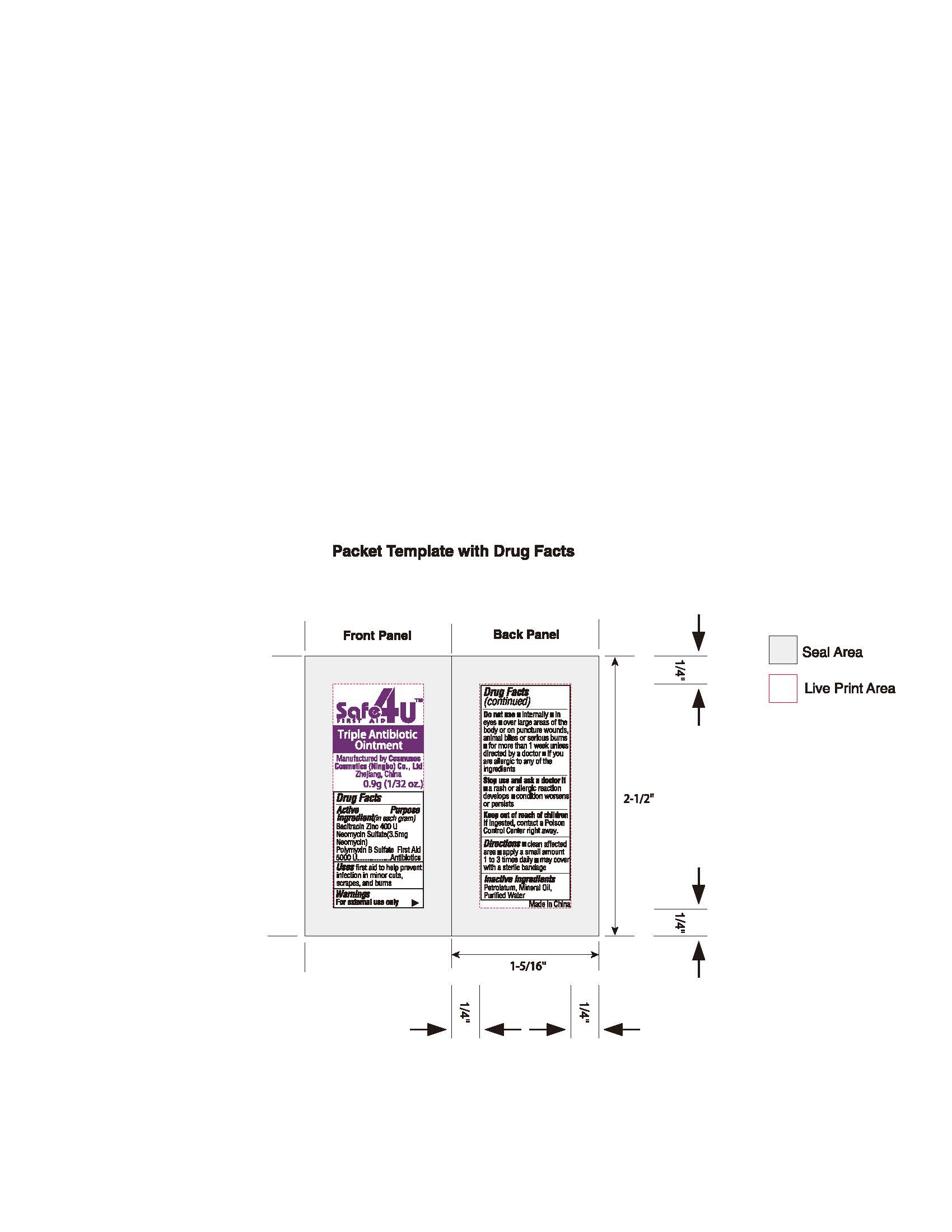 DRUG LABEL: triple antibiotic
NDC: 82953-013 | Form: OINTMENT
Manufacturer: Cosmuses Cosmetics (Ningbo) Co., Ltd.
Category: otc | Type: HUMAN OTC DRUG LABEL
Date: 20240104

ACTIVE INGREDIENTS: NEOMYCIN SULFATE 3.5 mg/1 g; POLYMYXIN B SULFATE 5000 U/1 g; BACITRACIN ZINC 400 U/1 g
INACTIVE INGREDIENTS: CETOSTEARYL ALCOHOL; GLYCERIN; WATER; POLYOXYL 20 CETOSTEARYL ETHER; ISOPROPYL MYRISTATE; ALOE VERA LEAF; PHENOXYETHANOL; EDETATE DISODIUM; ALPHA-TOCOPHEROL ACETATE

triple Antibiotic Ointment

Active Ingredients (in each gram)

Bacitracin Zinc 400U/g

Neomycin Sulfate (3.5mg Neomycin)

Polymyxin B Sulfate 5000U/g

Purpose

Antibiotics

Uses

First aid to help prevent infection in minor cuts, scrapes, and burns

Warnings

For external use only.

Do not use.

- in or near the eyes
- for diaper rash; ask a doctor

Ask a doctor before use if you are using any other hydrocortisone product

Stop use and ask doctor if

- condition worsens or if symptoms persist for more than 7 days
- symptoms last more than 7 days or clear up and occur again within a few days

Keep out of reach of children. If ingested, contact Poison Control Center right away.

Directions

- apply to affected area not more than 3 to 4 times daily
- children under 2 years do not use; ask a doctor

Other information

protect from Excessive Heat (40oC/ 104oF.)

Inactive Ingredients

Water, Cetearyl Alcohol, Glycerin, Glycerin, Ceteareth-20, Isopropyl Myristate, Disodium EDTA, Phenoxyethanol, Tocopheryl Acetate, Aloe Barbadensis Leaf Juice